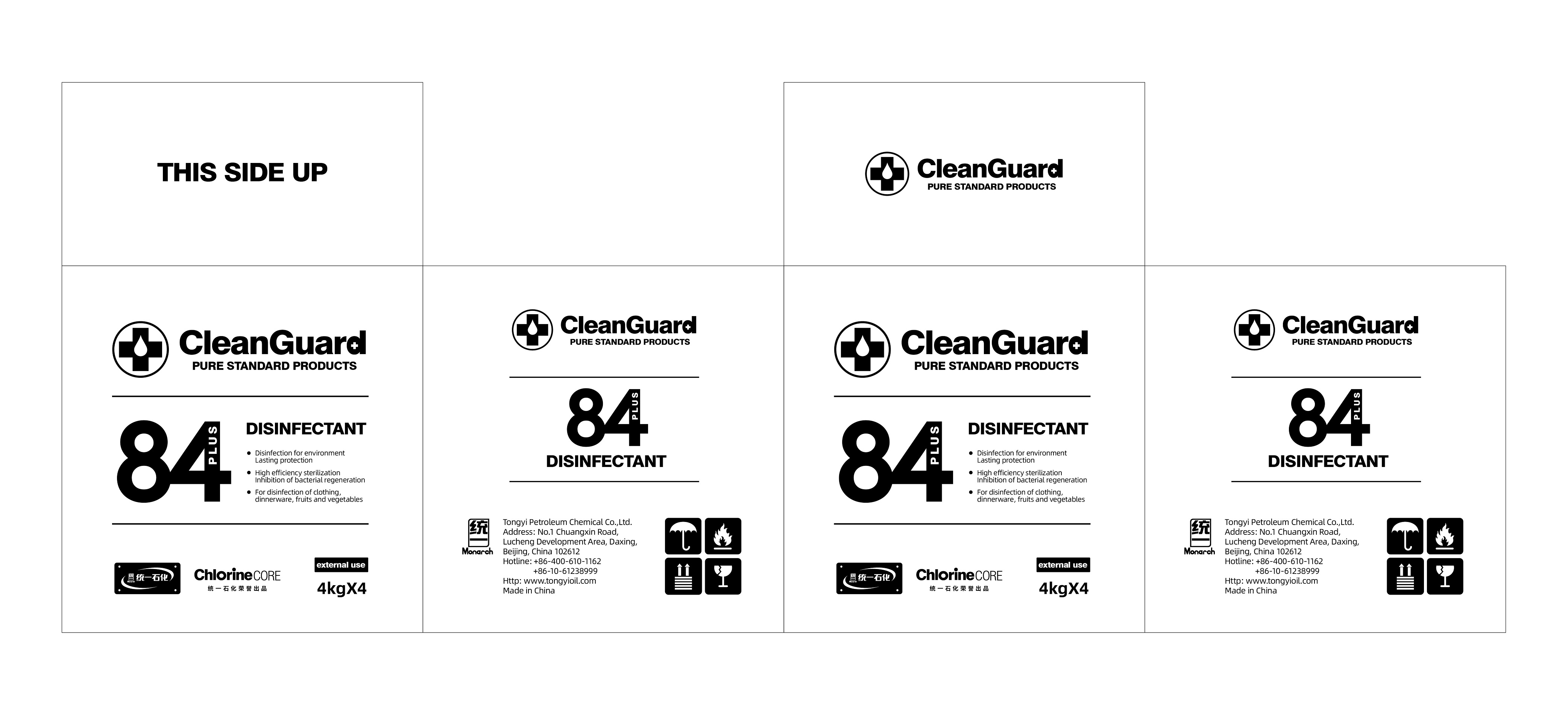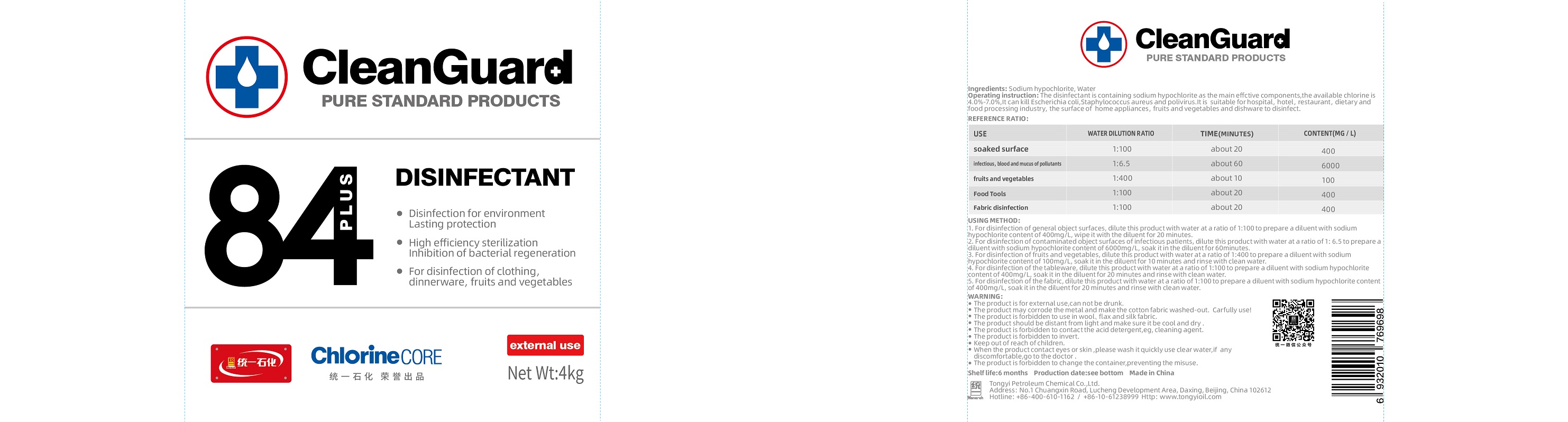 DRUG LABEL: TongYi CleanGuard 84 Disinfectant
NDC: 73681-1001 | Form: SOLUTION, CONCENTRATE
Manufacturer: Tongyi Petroleum Chemical Co., Ltd.
Category: otc | Type: HUMAN OTC DRUG LABEL
Date: 20200311

ACTIVE INGREDIENTS: SODIUM HYPOCHLORITE 2 kg/4 kg
INACTIVE INGREDIENTS: WATER 2 kg/4 kg

TongYi, 84 Disinfectant, 4kg *4

Active ingredient

Sodium hypochlorite

Inactive ingredient

Water

Purpose

Disinfection for environment; Lasting protection.
High efficiency sterilization; Inhibition of bacterial regeneration.
For disinfection of clothing, dinnerware, fruits and vegetables.

When using

Disinfection for environment; Lasting protection.
High efficiency sterilization; Inhibition of bacterial regeneration.
For disinfection of clothing, dinnerware, fruits and vegetables.

Do not use

Use only as directed.
Do not use for cases not directed.

Stop use

Stop use if the product's volatile gases cause discomfort, or if you experience respiratory irritation such as cough, asthma, or difficulty breathing.

Ask doctor

If using the product causes serious discomfort, ask or see your doctor.

Ask doctor/pharmacist

If using the product causes serious discomfort, ask or see your doctor/pharmacist.

Keep out of reach of children

Questions

Please contact with us at the phone number +86-10-61238999 when you have any questions.

Pregnancy or breast feeding

Pregnant or breast feeding women shall follow doctor advice.

Indications & usage

1, For disinfection of general object surfaces, dilute this product with water at a ratio of 1:100 to prepare a diluent with sodium hypochlorite content of 400mg/L, wipe it with the diluent for 20 minutes.
2, For disinfection of contaminated object surfaces of infectious patients, dilute this product with water at a ratio of 1:6.5 to prepare a diluent with sodium hypochlorite content of 6000mg/L, soak it in the diluent for 60 minutes.
3, For disinfectant of fruits and vegetables, dilute this product with water at a ration of 1:400 to prepare a diluent with sodium hypochlorite content of 100mg/L, soak it in the diluent for 10 minutes and rinse with clean water.
4, For disinfection of the tableware, dilute this product with water at a ratio of 1:100 to prepare a diluent with sodium hypochlorite content of 400mg/L, soak it with the diluent for 20 minutes and rinse with clean water.
5, For disinfection of the fabric, dilute this product with water at a ratio of 1:100 to prepare a diluent with sodium hypochlorite content of 400mg/L, soak it with the diluent for 20 minutes and rinse with clean water.

Dosage & administration

Use it as needed, after following the usage instructions.

For external use only.

Dosage forms & strengths

This product is liquid dosage form.
The active ingredient strength is 50%.

Warnings

* The product is for external use, can not be drunk.
* The product may corrode the metal and make the cotton fabric washed-out. Careful use!
* The product is forbidden to use in wool, flax and silk fabric.
* The product should be distant from light and make sure it be cool and dry.
* The product is forbidden to contact the acid detergent, eg, clean agent.
* The product is forbidden to invert.
* Keep out of reach of children.
* When the product contact eyes or skin, please wash it quickly use clean water, if any dis comfortable, go to the doctor.
* The product is forbidden to change the container, preventing the misuse.

Package label. Principal display panel

Drum Label - Container Label

Box Label - Package Label